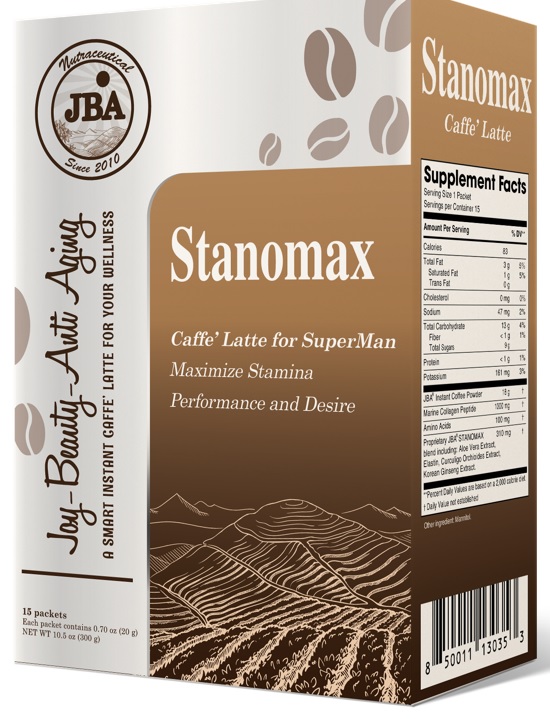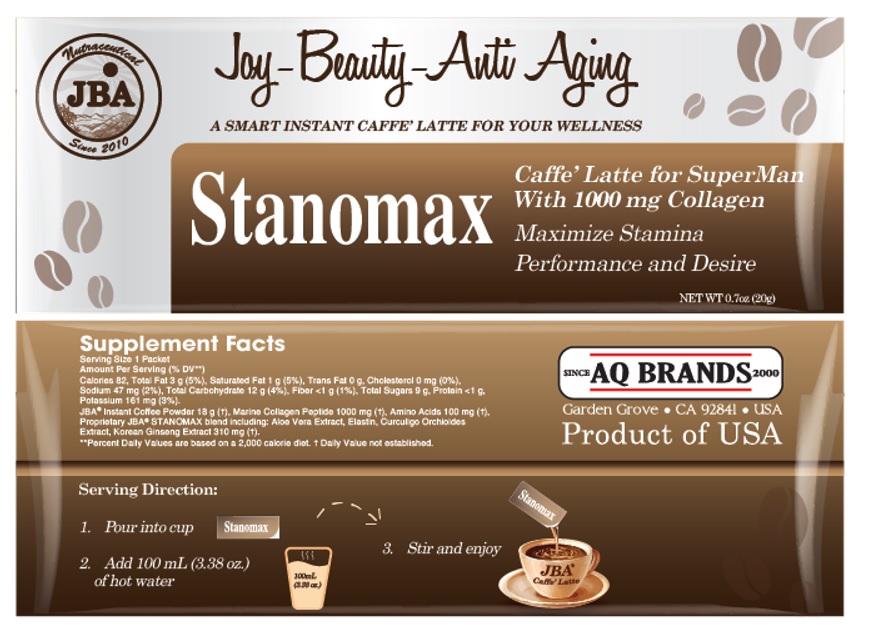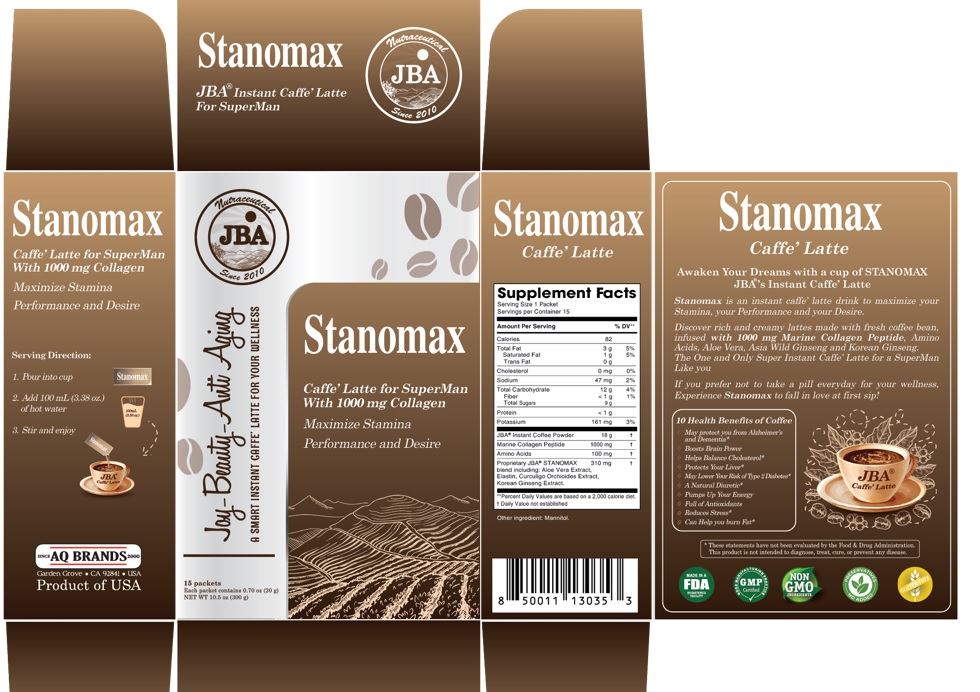 DRUG LABEL: JBA STANOMAX Caffe Latte
NDC: 13411-877 | Form: POWDER
Manufacturer: Advanced Pharmaceutical Services, Inc. Dba Affordable Quality Pharmaceuticals
Category: other | Type: DIETARY SUPPLEMENT
Date: 20230221

ACTIVE INGREDIENTS: POTASSIUM 161 mg/20 g; COFFEE BEAN 18 g/20 g; MARINE COLLAGEN, SOLUBLE 1000 mg/20 g; AMINO ACIDS, SOURCE UNSPECIFIED 100 mg/20 g; ALOE VERA LEAF 100 mg/20 g; ELASTIN BOVINE 10 mg/20 g; CURCULIGO ORCHIOIDES WHOLE 100 mg/20 g; ASIAN GINSENG 100 mg/20 g
INACTIVE INGREDIENTS: MANNITOL

Identity

Dietary supplement

Direction

1. Pour into cup
2. Add 100 mL (3.38 oz.) of hot water
3. Stir and enjoy.

Safe handling warning

JBA® STANOMAX Caffe’ Latte for Superman With 1000mg Collagen
Maximize Stamina
Performance and Desire

Awaken Your Dreams with a cup of STANOMAX JBA®'s Instant Caffe’ Latte

Stanomax is an instant caffe’ latte drink to maximize your Stamina, your Performance and your Desire.
Discover rich and creamy lattes made with fresh coffee bean, infused with 1000 mg Marine Collagen Peptide , Amino Acids, Aloe Vera, Asia Wild Ginseng and Korean Ginseng.

The One and Only Super Instant Caffe’ Latte for a SuperMan Like you

If you prefer not to take a pill everyday for your wellness,
Experience Stanomax to fall in love at first sip.

10 Health Benefits of Coffee
- May protect you from Alzheimer’s and Dementia*
- Boosts Brain Power
- Helps Balance Cholesterol*
- Protects Your Liver*
- May Lower Your Risk of Type 2 Diabetes*
- A Natural Diuretic*
- Pumps Up Your Energy
- Full of Antioxidants
- Reduces Stress*
- Can Help you burn Fat*
* These statements have not been evaluated by the Food & Drug Administration. This product is not intended to diagnose, treat, cure, or prevent any disease.